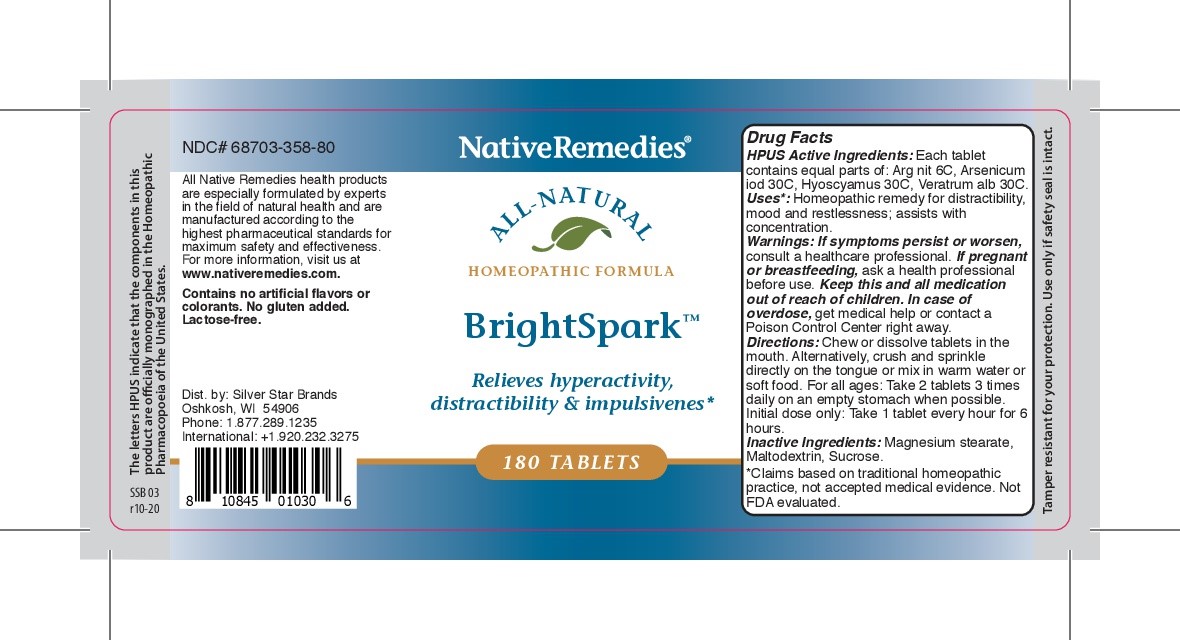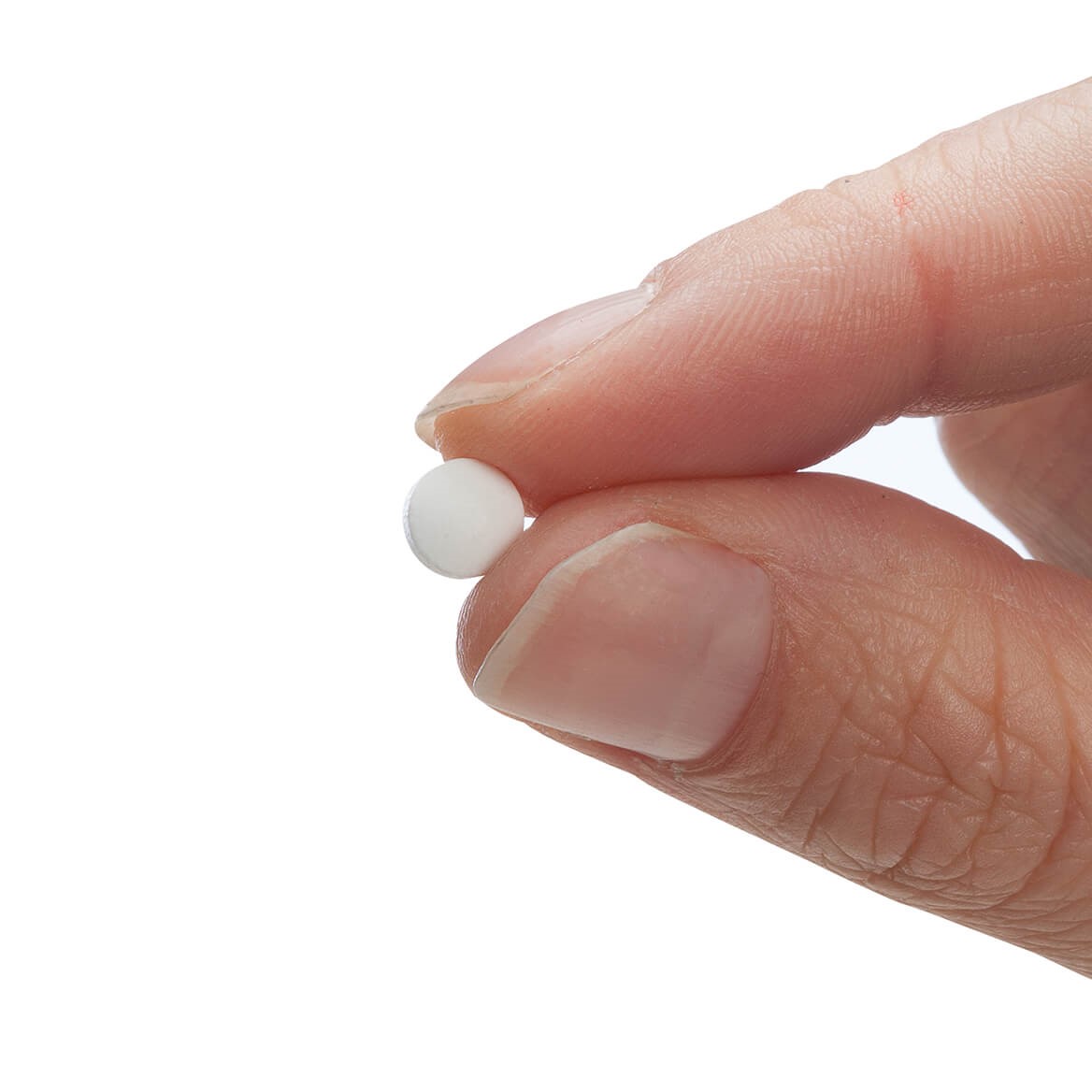 DRUG LABEL: Brightspark
NDC: 68703-358 | Form: TABLET
Manufacturer: Silver Star Brands
Category: homeopathic | Type: HUMAN OTC DRUG LABEL
Date: 20250101

ACTIVE INGREDIENTS: SILVER NITRATE 6 [hp_C]/180 1; VERATRUM ALBUM ROOT 30 [hp_C]/180 1; ARSENIC TRIIODIDE 30 [hp_C]/180 1; HYOSCYAMUS NIGER LEAF 30 [hp_C]/180 1
INACTIVE INGREDIENTS: MALTODEXTRIN; MAGNESIUM STEARATE; SUCROSE

NativeRemedies® BrightSpark™ Tablets

HPUS Active Ingredients: Each tablet contains equal parts of: Arg nit 6C, Arsenicum iod 30C, Hyoscyamus 30C, Veratrum alb 30C.

Uses*

Uses*: Homeopathic remedy for distractibility, mood, and restlessness; assists with concentration.

*Claims based on traditional homeopathic practice, not accepted medical evidence. Not evaluated by the FDA.

Warnings

Warnings: If symptoms persist or worsen, consult a healthcare professional. If pregnant or breastfeeding, ask a health professional before use. Keep this and all medication out of reach of children. In case of overdose, get medical help or contact a Poison Control Center right away.

Directions

Directions: Chew or dissolve tablets in the mouth. Alternatively, crush and sprinkle directly on the tongue or mix in warm water or soft food. For all ages: Take 2 tablets 3 times daily on an empty stomach when possible.

Initial dose only: Take 1 tablet every hour for 6 hours.

OTHER SAFETY INFORMATION

Tamper resistant for your proection. Use only if saftey seal is intact.

Contains no artificial flavors or colorants. No gluten added. Lactose-free.

Inactive Ingredients

Inactive Ingredients: Magnesium stearat, Maltodextrin, Sucrose.

KEEP OUT OF REACH OF CHILDREN

Keep this and all medication out of reach of children.

PREGNANCY OR BREAST FEEDING

If pregnant or breastfeeding, ask a health professional before use.

PURPOSE

Relieves hyperactivity distractibility & impulsiveness.